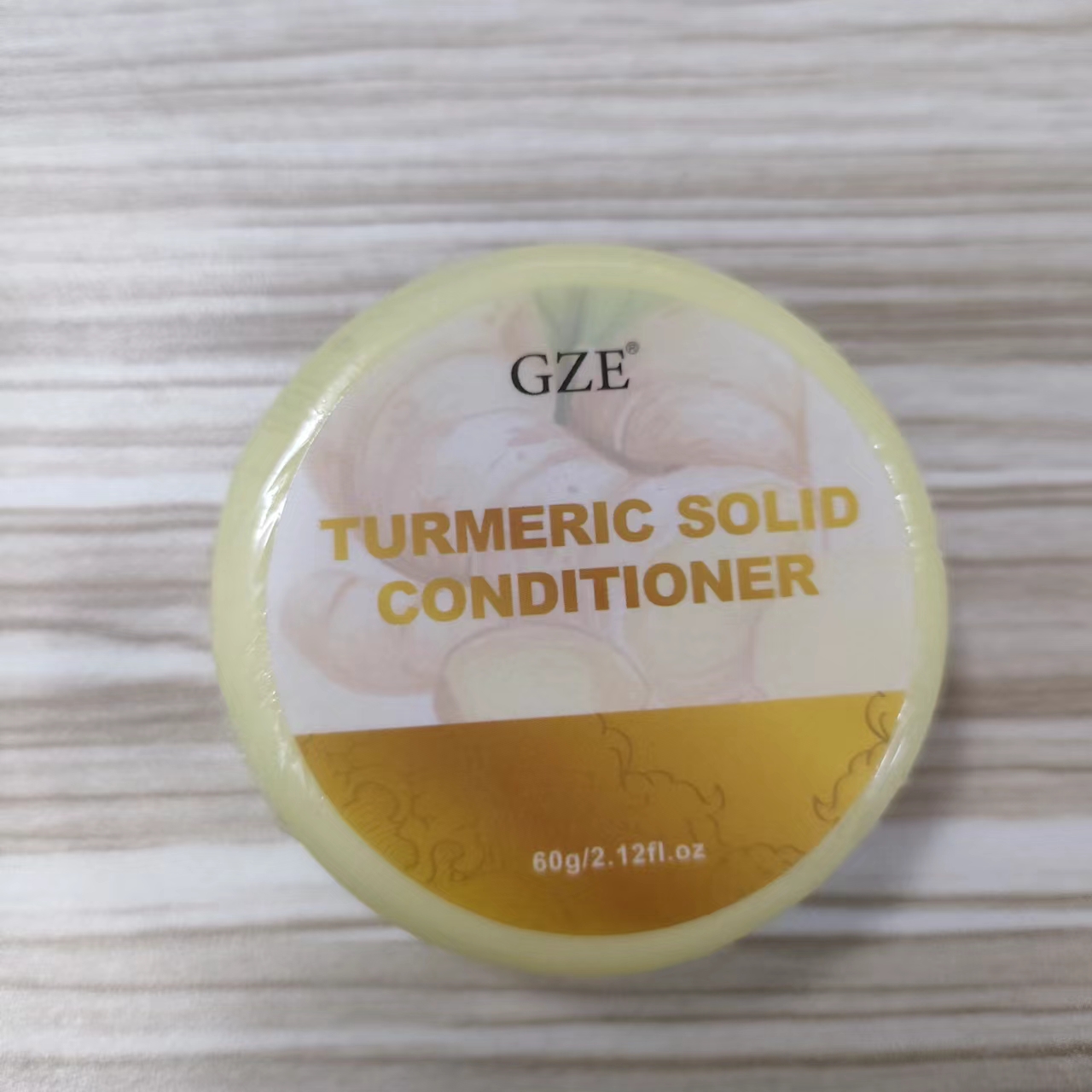 DRUG LABEL: GZE TURMERIC SOLID CONDITIONER
NDC: 74458-111 | Form: SOAP
Manufacturer: Guangzhou Yilong Cosmetics Co., Ltd
Category: otc | Type: HUMAN OTC DRUG LABEL
Date: 20241024

ACTIVE INGREDIENTS: ROSMARINUS OFFICINALIS (ROSEMARY) LEAF EXTRACT 15 g/100 g
INACTIVE INGREDIENTS: OLEA EUROPAEA (OLIVE) FRUIT OIL; COCOS NUCIFERA (COCONUT) OIL; SIMMONDSIA CHINENSIS (JOJOBA) SEED OIL; VITIS VINIFERA (GRAPE) SEED OIL; CITRUS LIMON (LEMON) FRUIT EXTRACT; CURCUMA LONGA (TURMERIC) ROOT EXTRACT

GZE TURMERIC SOLID CONDITIONER

ACTIVE INGREDIENT

Rosmarinus Officinalis (Rosemary) Leaf Extract 15%

INACTIVE INGREDIENT

Curcuma Longa (Turmeric) Root Extract

Olea Europaea (Olive) Fruit Oil

Cocos Nucifera (Coconut) Oil

Citrus Limon (Lemon) Fruit Extract

Simmondsia Chinensis (Jojoba) Seed Oil

Vitis Vinifera (Grape) Seed Oil

PURPOSE

Make hair healthier.

INDICATIONS AND USAGE

After shampooing,wet this turmeric solid conditioner bar and slide down your hair 5 -6 times.Massage the goodness into your hair and leave for 1-2 minutes. Rinse thoroughly for soft hair.

WARNINGS

For external use only.

Stop use and ask a doctor if rash occurs.

Do not use on damaged or broken skin.

When using this product keep out of eyes. Rinse with water to remove.

Keep out of reach of children. If swallowed, get medical help or contact a Poison Control Center right away.

DOSAGE AND ADMINISTRATION

After shampooing,wet this turmeric solid conditioner bar and slide down your hair 5 -6 times.Massage the goodness into your hair and leave for 1-2 minutes. Rinse thoroughly for soft hair.